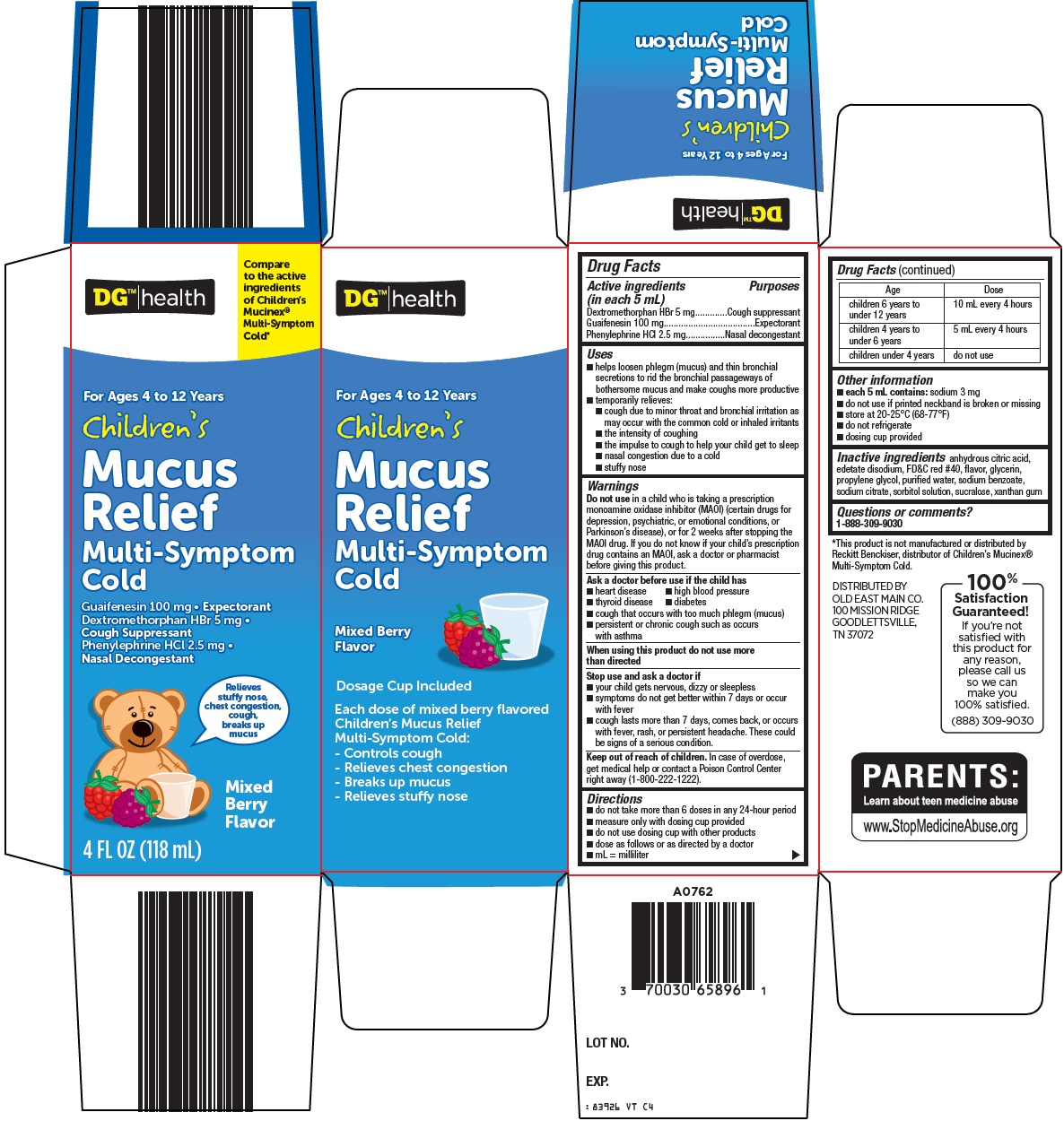 DRUG LABEL: dg health childrens mucus relief
NDC: 55910-839 | Form: SOLUTION
Manufacturer: Dolgencorp Inc
Category: otc | Type: HUMAN OTC DRUG LABEL
Date: 20241112

ACTIVE INGREDIENTS: DEXTROMETHORPHAN HYDROBROMIDE 5 mg/5 mL; GUAIFENESIN 100 mg/5 mL; PHENYLEPHRINE HYDROCHLORIDE 2.5 mg/5 mL
INACTIVE INGREDIENTS: ANHYDROUS CITRIC ACID; EDETATE DISODIUM; FD&C RED NO. 40; GLYCERIN; PROPYLENE GLYCOL; WATER; SODIUM BENZOATE; SODIUM CITRATE, UNSPECIFIED FORM; SORBITOL; SUCRALOSE; XANTHAN GUM

Dolgencorp, LLC Children’s Mucus Relief Drug Facts

Active ingredients (in each 5 mL)

Dextromethorphan HBr 5 mg

Guaifenesin 100 mg

Phenylephrine HCl 2.5 mg

Purposes

Cough suppressant

Expectorant

Nasal decongestant

Uses

- helps loosen phlegm (mucus) and thin bronchial secretions to rid the bronchial passageways of bothersome mucus and make coughs more productive
- temporarily relieves:
- cough due to minor throat and bronchial irritation as may occur with the common cold or inhaled irritants
- the intensity of coughing
- the impulse to cough to help your child get to sleep
- nasal congestion due to a cold
- stuffy nose

Warnings

Do not use

in a child who is taking a prescription monoamine oxidase inhibitor (MAOI) (certain drugs for depression, psychiatric, or emotional conditions, or Parkinson’s disease), or for 2 weeks after stopping the MAOI drug. If you do not know if your child’s prescription drug contains an MAOI, ask a doctor or pharmacist before giving this product.

Ask a doctor before use if the child has

- heart disease
- high blood pressure
- thyroid disease
- diabetes
- cough that occurs with too much phlegm (mucus)
- persistent or chronic cough such as occurs with asthma

When using this product

do not use more than directed

Stop use and ask a doctor if

- your child gets nervous, dizzy or sleepless
- symptoms do not get better within 7 days or occur with fever
- cough lasts more than 7 days, comes back, or occurs with fever, rash, or persistent headache. These could be signs of a serious condition.

Keep out of reach of children.

In case of overdose, get medical help or contact a Poison Control Center right away (1-800-222-1222).

Directions

- do not take more than 6 doses in any 24-hour period
- measure only with dosing cup provided
- do not use dosing cup with other products
- dose as follows or as directed by a doctor
- mL = milliliter

Age | Dose
children 6 years to under 12 years | 10 mL every 4 hours
children 4 years to under 6 years | 5 mL every 4 hours
children under 4 years | do not use

Other information

- each 5 mL contains: sodium 3 mg
- do not use if printed neckband is broken or missing
- store at 20-25°C (68-77°F)
- do not refrigerate
- dosing cup provided

Inactive ingredients

anhydrous citric acid, edetate disodium, FD&C red #40, flavor, glycerin, propylene glycol, purified water, sodium benzoate, sodium citrate, sorbitol solution, sucralose, xanthan gum

Questions or comments?

1-888-309-9030

Package/Label Principal Display Panel

DG™|health

Compare to the active ingredients of Children’s Mucinex® Multi-Symptom Cold

For Ages 4 to 12 Years

Children’s Mucus Relief

Multi-Symptom Cold

Guaifenesin 100 mg • Expectorant

Dextromethorphan HBr 5 mg • Cough Suppressant

Phenylephrine HCl 2.5 mg • Nasal Decongestant

Relieves stuffy nose, chest congestion, cough, breaks up mucus

Mixed Berry Flavor

4 FL OZ (118 mL)